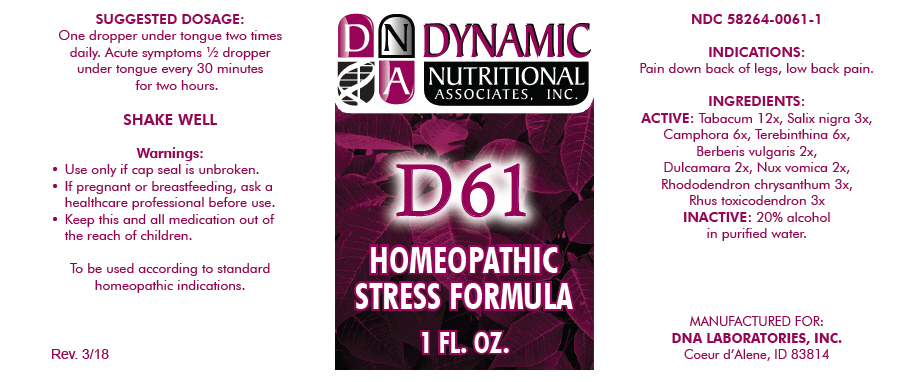 DRUG LABEL: D-61
NDC: 58264-0061 | Form: SOLUTION
Manufacturer: DNA Labs, Inc.
Category: homeopathic | Type: HUMAN OTC DRUG LABEL
Date: 20250113

ACTIVE INGREDIENTS: TOBACCO LEAF 12 [hp_X]/1 mL; SALIX NIGRA BARK 3 [hp_X]/1 mL; CAMPHOR (NATURAL) 6 [hp_X]/1 mL; TURPENTINE OIL 6 [hp_X]/1 mL; BERBERIS VULGARIS ROOT BARK 2 [hp_X]/1 mL; SOLANUM DULCAMARA WHOLE 2 [hp_X]/1 mL; STRYCHNOS NUX-VOMICA SEED 2 [hp_X]/1 mL; RHODODENDRON AUREUM LEAF 3 [hp_X]/1 mL; TOXICODENDRON PUBESCENS LEAF 3 [hp_X]/1 mL
INACTIVE INGREDIENTS: ALCOHOL; WATER

D-61

NDC 58264-0061-1

INDICATIONS

PURPOSE

Pain down back of legs, low back pain.

INGREDIENTS

ACTIVE

Tabacum 12x, Salix nigra 3x, Camphora 6x, Terebinthina 6x, Berberis vulgaris 2x, Dulcamara 2x, Nux vomica 2x, Rhododendron chrysanthum 3x, Rhus toxicodendron 3x

INACTIVE

20% alcohol in purified water.

SUGGESTED DOSAGE

One dropper under tongue two times daily. Acute symptoms ½ dropper under tongue every 30 minutes for two hours.

STORAGE AND HANDLING

SHAKE WELL

Warnings

- Use only if cap seal is unbroken.

PREGNANCY OR BREAST FEEDING

- If pregnant or breastfeeding, ask a healthcare professional before use.

KEEP OUT OF REACH OF CHILDREN

- Keep this and all medication out of the reach of children.

To be used according to standard homeopathic indications.

PRINCIPAL DISPLAY PANEL - 1 FL. OZ. Bottle Label

DYNAMIC
NUTRITIONAL
ASSOCIATES, INC.

D 61

HOMEOPATHIC
STRESS FORMULA

1 FL. OZ.